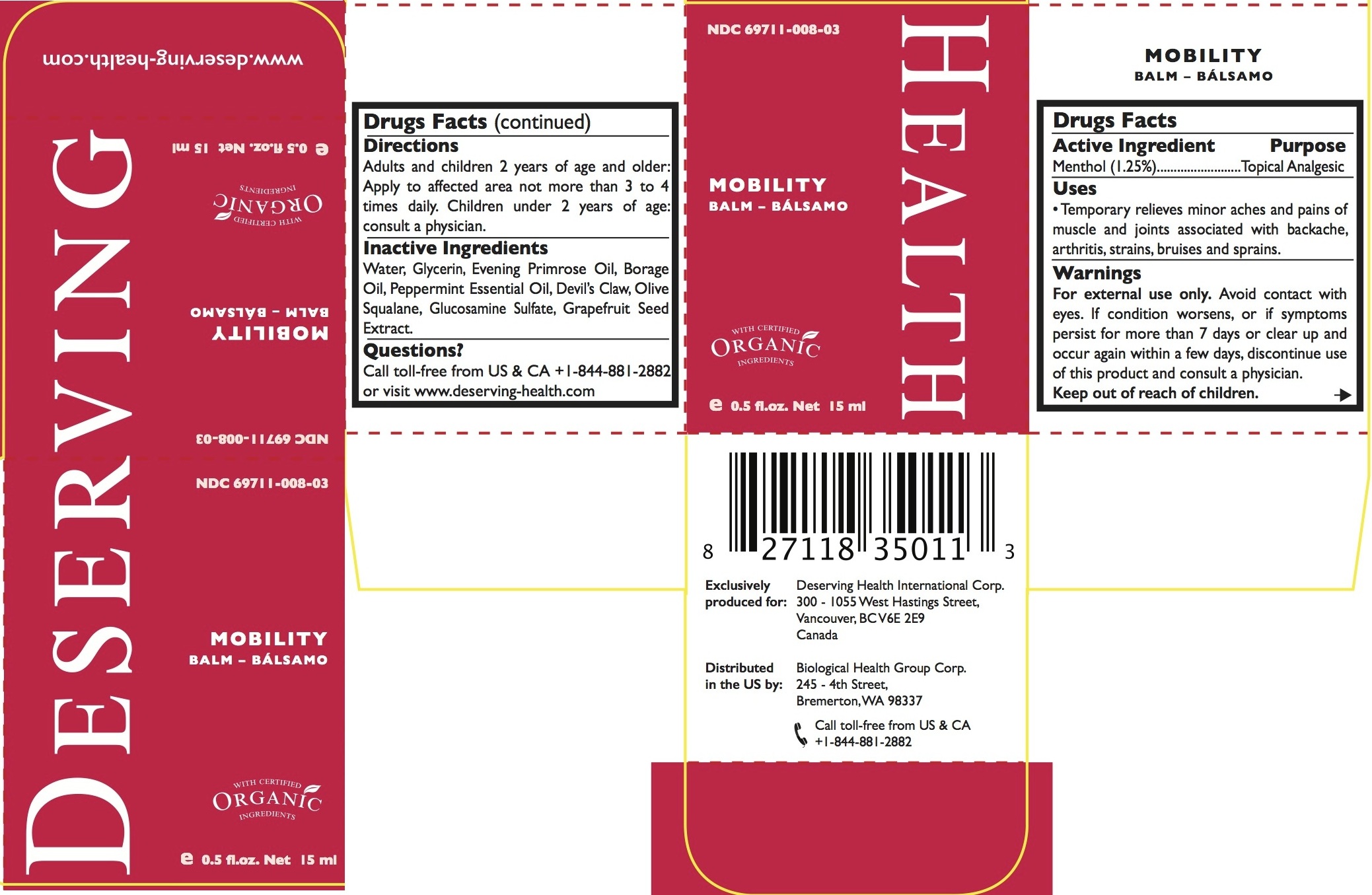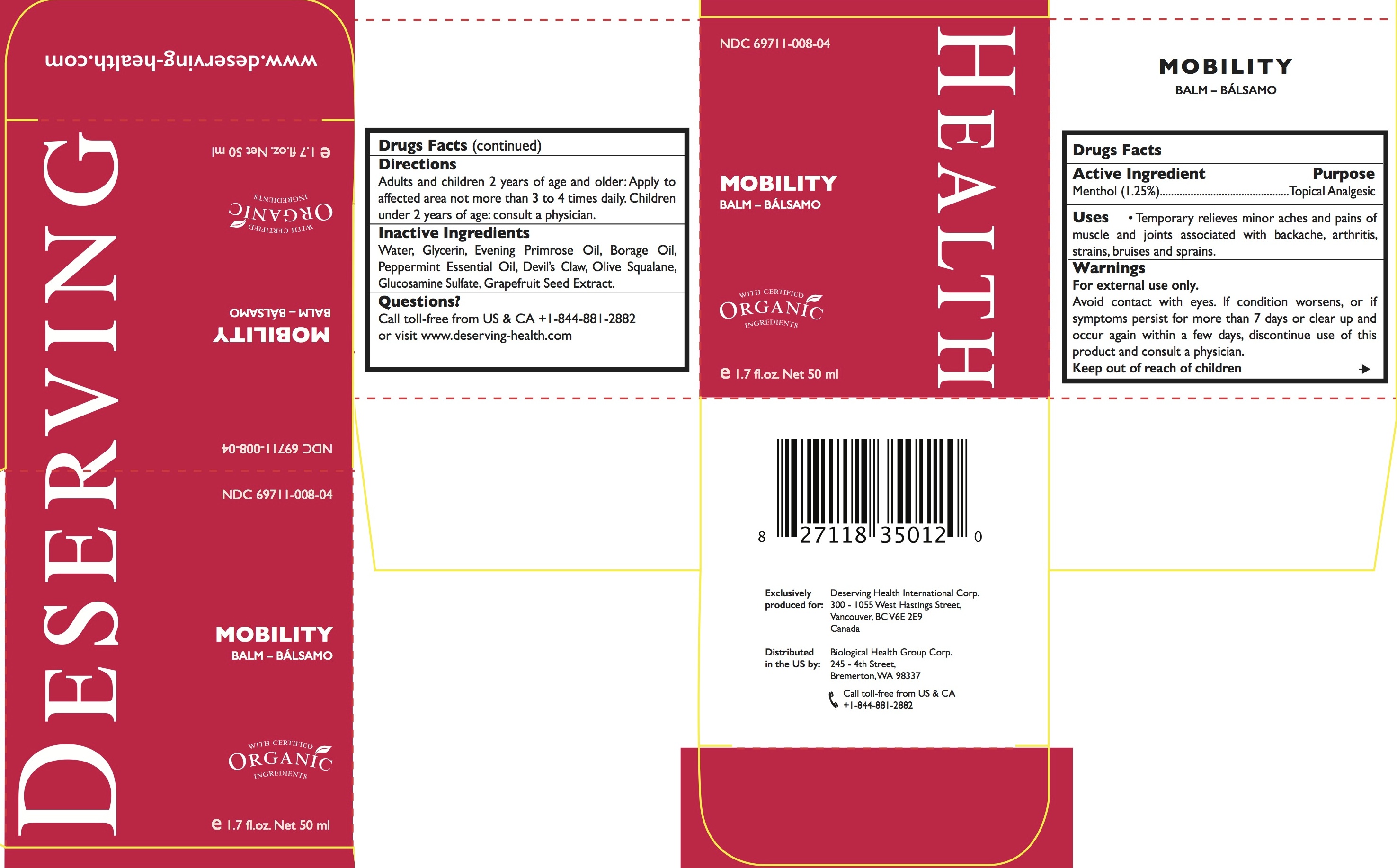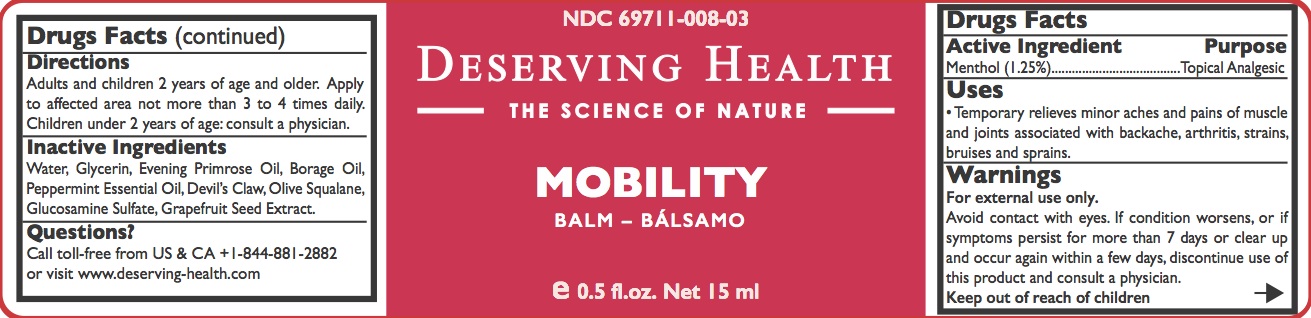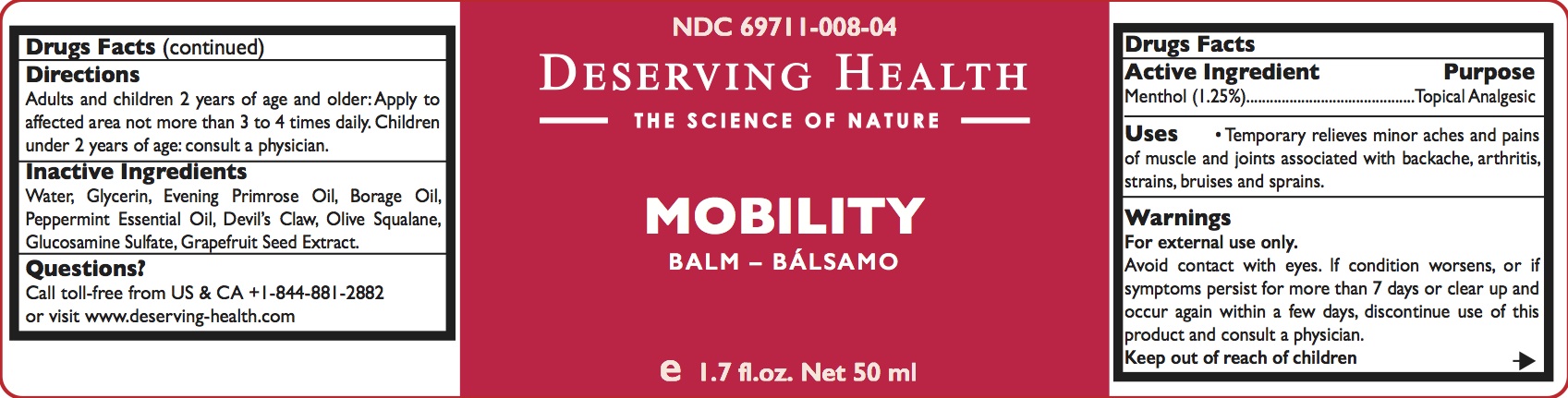 DRUG LABEL: MOBILITY
NDC: 69711-008 | Form: CREAM
Manufacturer: Biological Health Group Corporation
Category: otc | Type: HUMAN OTC DRUG LABEL
Date: 20150501

ACTIVE INGREDIENTS: MENTHOL 1.5 g/100 mL
INACTIVE INGREDIENTS: GLYCERIN; EVENING PRIMROSE OIL; BORAGE OIL; PEPPERMINT OIL; HARPAGOPHYTUM PROCUMBENS ROOT; WATER; SQUALANE; GLUCOSAMINE SULFATE; CITRUS PARADISI SEED

MOBILITY
BALM - BÁLSAMO

Drug Facts

Active Ingredient

Menthol 1.5%

Purpose

Topical analgesic

Uses

Temporary relieves minor aches and pains of muscle and joints associated with backache, arthritis, strains, bruises and sprains.

Warnings

For external use only

When using this product

Avoid contact with eyes.

Stop use and ask a doctor if condition worsens, or if symptoms persist for more than 7 days or clear up and occur again within a few days, discontinue use of this product and consult a physician.

Keep out of reach of children.

Directions

Adults and children 2 years of age and older: Apply to affected areas not more than 3 to 4 times daily.

Children under 2 years of age: consult a physician.

Inactive ingredients

Water, Glycerine, Evening Primrose Oil, Borage Oil, Peppermint oil, Devil’s Claw, Olive Squalane, Glucosamine Sulfate, Grapefruit Seed Extract.

Distributed in the US by:

Biological Health Group Corp.
245 - 4th Street, Bremerton, WA 98337
Call toll-free from US & Canada +1-844-881-2882

PRINCIPAL DISPLAY PANEL

15mL Box

50 mL Box

Questions?

Call toll-free from US & Canada +1-844-881-2882
or visit www.deserving-health.com